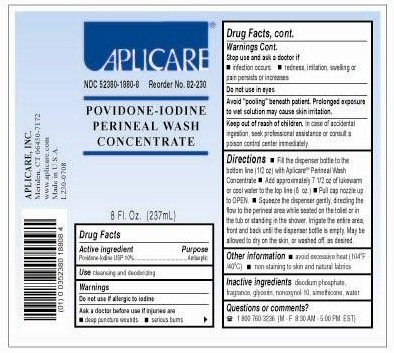 DRUG LABEL: Aplicare Povidone-iodine Perineal Wash 
NDC: 52380-1880 | Form: LIQUID
Manufacturer: Aplicare, Inc.
Category: otc | Type: HUMAN OTC DRUG LABEL
Date: 20100331

ACTIVE INGREDIENTS: Povidone-iodine 10 1/100 g
INACTIVE INGREDIENTS: Nonoxynol-10; Glycerin; Silicon Dioxide; Dimethicone; Sodium Phosphate, Dibasic Anhydrous; Water

Drug Facts

ACTIVE INGREDIENT

Povidone-iodine

PURPOSE

Antiseptic

Stop use and ask a doctor if

- infection occurs
- redness, irritation, swelling or pain persists or increases

Ask a doctor before use if injuries are

- deep puncture wounds
- serious burns

Do not use if allergic to iodine.

Do not use in eyes.

WARNINGS

Avoid "pooling" beneath patient. Prolonged exposure to wet solution may cause skin irritation.

Keep out of reach of children. In case of accidental ingestion, seek professional assistance or consult a poison control center immediately.

Bottle Label